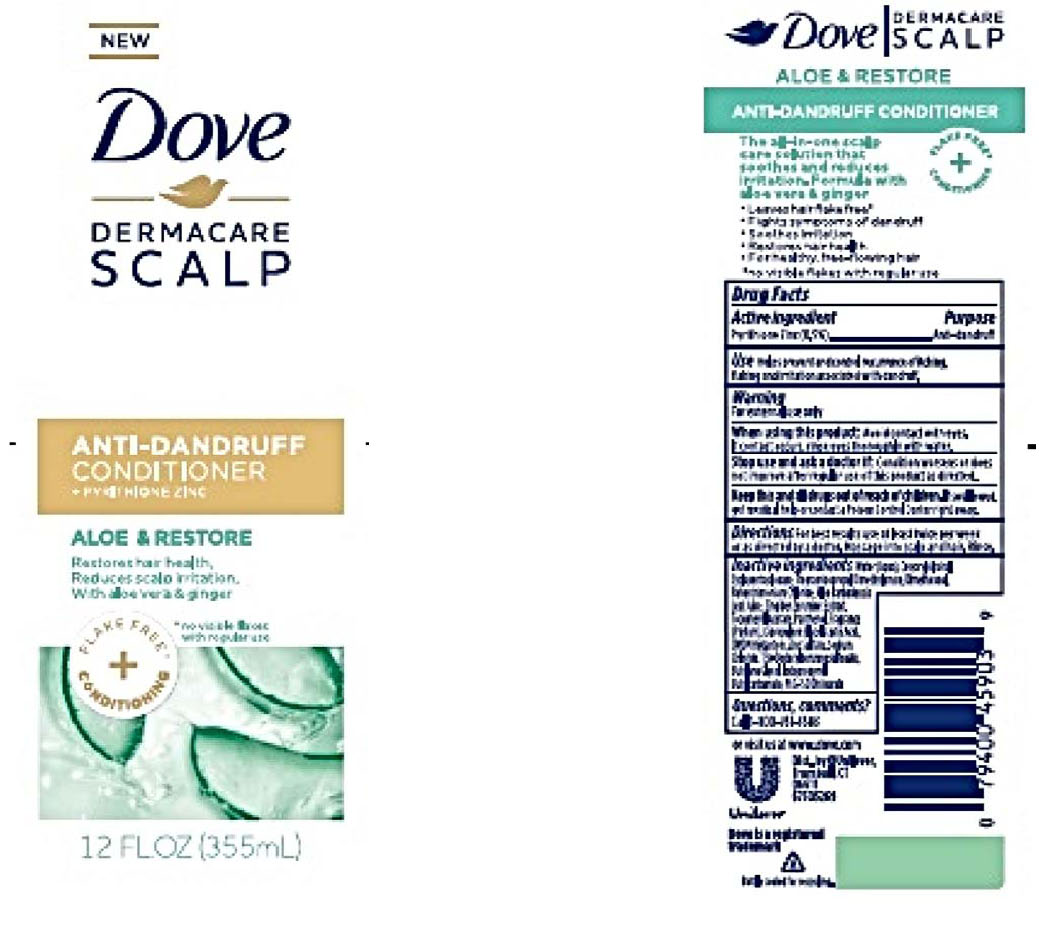 DRUG LABEL: Dove
NDC: 64942-1620 | Form: LIQUID
Manufacturer: Conopco, Inc. d/b/a/ Unilever
Category: otc | Type: HUMAN OTC DRUG LABEL
Date: 20221207

ACTIVE INGREDIENTS: PYRITHIONE ZINC 0.5 g/100 mL
INACTIVE INGREDIENTS: ALOE VERA LEAF; WATER; CETOSTEARYL ALCOHOL; CYCLOMETHICONE 5; STEARAMIDOPROPYL DIMETHYLAMINE; DIMETHICONOL (40 CST); BEHENTRIMONIUM CHLORIDE; .ALPHA.-TOCOPHEROL ACETATE, D-; DIPROPYLENE GLYCOL; LACTIC ACID, UNSPECIFIED FORM; DMDM HYDANTOIN; ZINC SULFATE, UNSPECIFIED FORM; SODIUM CHLORIDE; TRIETHANOLAMINE DODECYLBENZENESULFONATE; BUTYLENE GLYCOL; IODOPROPYNYL BUTYLCARBAMATE; PEG-150 DISTEARATE; PANTHENOL

Dove Dermacare Scalp Aloe & Restore Anti-Dandruff Conditioner

DOVE DERMACARE SCALP ALOE & RESTORE ANTI-DANDRUFF CONDITIONER - pyrithione zinc liquid

Dove Dermacare Scalp Aloe & Restore Anti-Dandruff Conditioner

Drug Facts

Active ingredient
Pyrithione Zinc (0.5%)

Purpose

Anti-dandruff

Use

• Helps prevent and control recurrence of itching, flaking and irritation associated with dandruff.

Warning

• For external use only
• When using this product: Avoid contact with eyes. If contact occurs, rinse eyes thoroughtly with water.
• Stop use and ask a doctor if: Condition worsens or does not improve after regular use of this product as directed.

KEEP OUT OF REACH OF CHILDREN

• Keep this and all drugs out of reach of children.
If swallowed, get medical help or contact a Poison Control Center right away.

Directions

For best results use at least twice per week or as directed by a doctor. Massage into scalp and hair. Rinse.

Inactive Ingredients

Water(Aqua), Cetearyl Alcohol, Cyclopentasiloxne, Stearamidopropyl Dimethylamine, Dimethiconol, Behentrimonium Chloride, Aloe Barbadensis Leaf Juice, Zingiber Zerumbet Extract, Tocopheryl Acetate, Panthenol, Fragrance(Parfum), Dipropylene Glycol, Lactic Acid, DMDM Hydantoin, Zinc Sulfate, Sodium Chloride, TEA-Dodecylbenzenesulfonate, Butylene Glycol, Iodopropynyl Butylcarbamate, PEG-150 Distearate.

Questions?

Call 1-800-761-3683